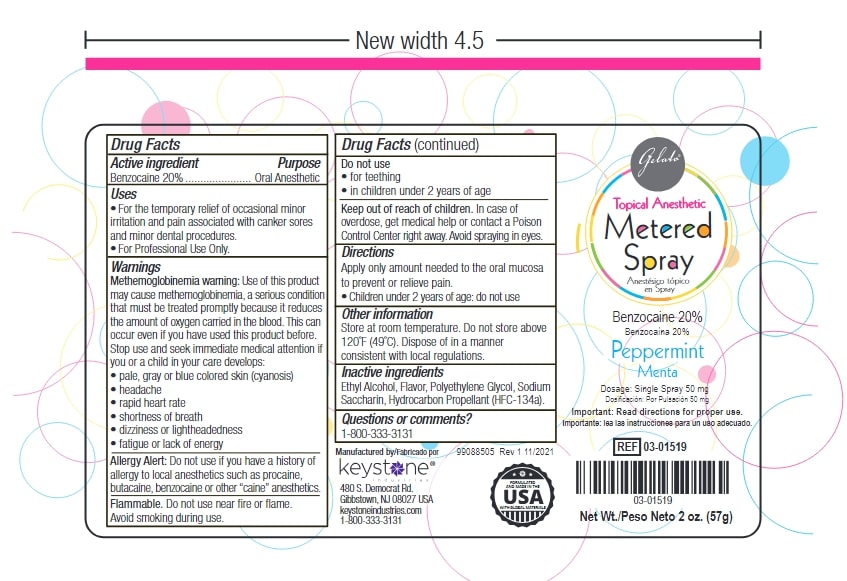 DRUG LABEL: Gelato Topical Anesthetic
NDC: 68400-323 | Form: SPRAY, METERED
Manufacturer: Mycone Dental Supply Co., Inc DBA Keystone Industries and Deepak Products Inc
Category: otc | Type: HUMAN OTC DRUG LABEL
Date: 20240411

ACTIVE INGREDIENTS: BENZOCAINE 11.4 g/57 g
INACTIVE INGREDIENTS: POLYETHYLENE GLYCOL 400; SACCHARIN SODIUM; ALCOHOL; ISOBUTANE; PROPANE

Active Ingredient

Benzocaine 20%

Purpose

Oral Anesthetic

Uses

- For the temporary relief of occasional minor irritation and pain associated with canker sores and minor dental procedures.
- For Professional Use Only.

Warnings

Methemoglobinemia warning: Use of this product may cause methemoglobinemia, a serious condition that must be treated promptly because it reduces the amount of oxygen carried in the blood. This can occur even if you have used this product before. Stop use and seek immediate medical attention if you or a child in your care develops:

- pale, gray or blue colored skin (cyanosis)
- headache
- rapid heart rate
- shortness of breath
- dizziness or lightheadedness
- fatigue or lack of energy

Allergy Alert: Do not use on patients with a history of allergies to local anesthetics such as procaine, butacaine, benzocaine or other "caine" anesthetics.

Flammable. Do not use near fire or flame. Avoid smoking during use.

Do not use

- for teething
- in children under 2 years of age

Keep out of reach of children.

In case of overdose, get medical help or contact a Poison Control Center right away. Avoid spraying in eyes.

Directions

Apply only amount needed to the oral mucosa to prevent or relieve pain.

- Children under 2 years of age: do not use

Other information

Store at room temperature. Do not store above 120°F (49°C). Dispose of in a manner consistent with local regulations.

Inactive Ingredients

Ethyl Alcohol, Flavor, Polyethylene Glycol, Sodium Saccharin, Hydrocarbon Propellant (Isobutane and propane).

Questions or comments?

1-800-333-3131